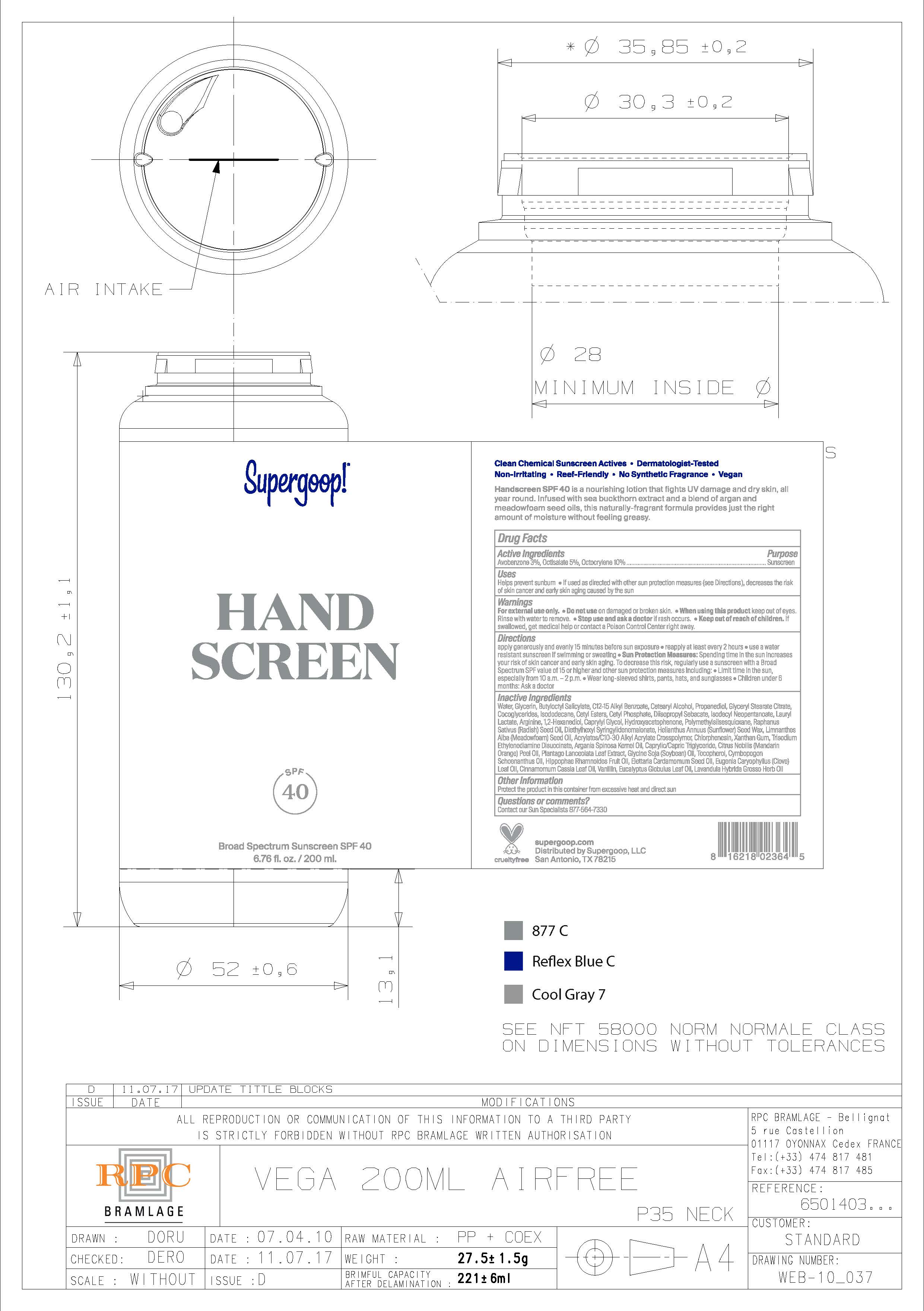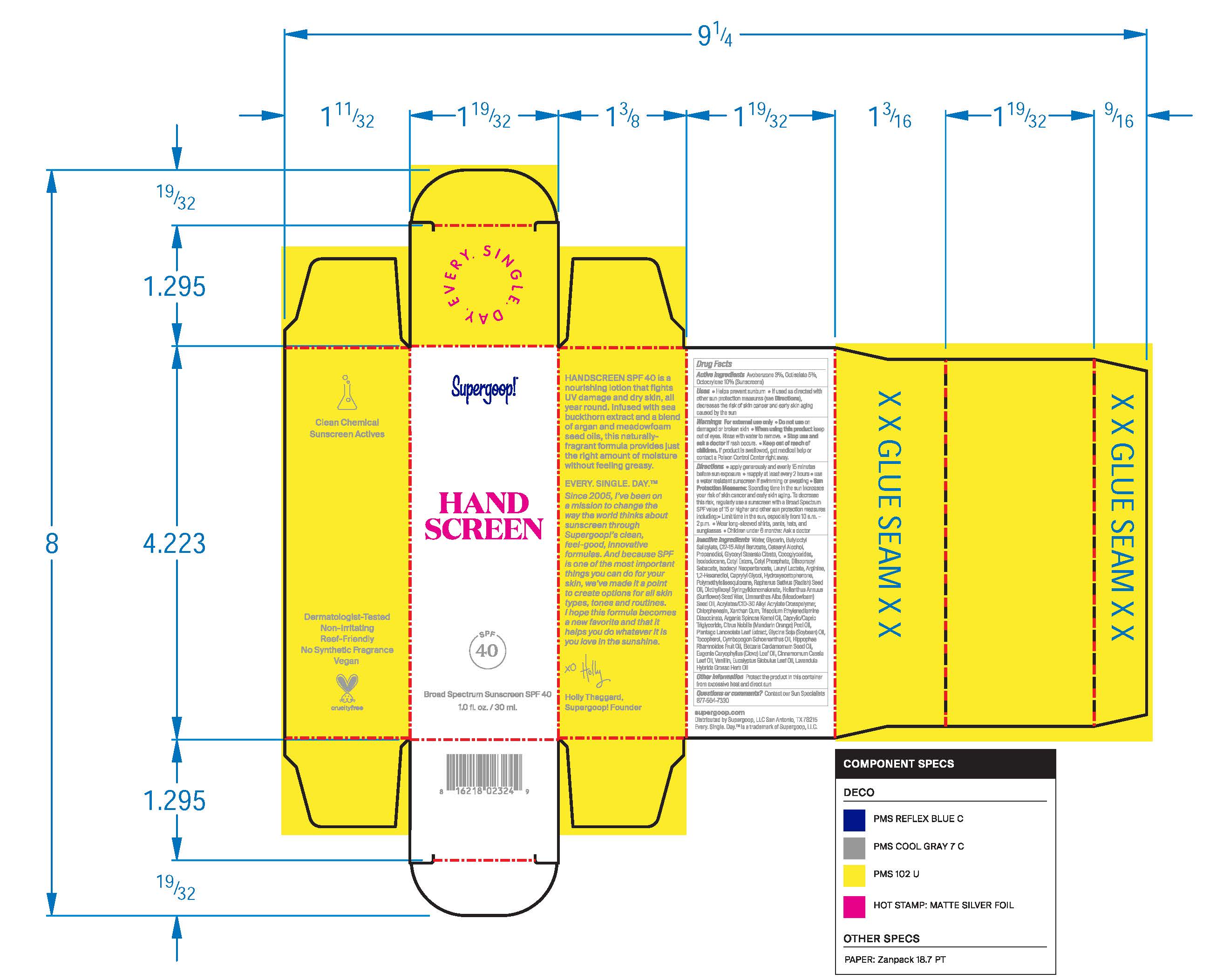 DRUG LABEL: Hand Screen Broad Spectrum Sunscreen SPF 40
NDC: 75936-151 | Form: LOTION
Manufacturer: Supergoop, LLC
Category: otc | Type: HUMAN OTC DRUG LABEL
Date: 20241204

ACTIVE INGREDIENTS: OCTISALATE 5 g/100 mL; AVOBENZONE 3 g/100 mL; OCTOCRYLENE 10 g/100 mL
INACTIVE INGREDIENTS: MANDARIN OIL; SOYBEAN OIL; TOCOPHEROL; CYMBOPOGON SCHOENANTHUS OIL; ISODECYL NEOPENTANOATE; CHLORPHENESIN; CETYL ESTERS WAX; GLYCERIN; ALKYL (C12-15) BENZOATE; ISODODECANE; MEADOWFOAM SEED OIL; HIPPOPHAE RHAMNOIDES FRUIT OIL; CARDAMOM OIL; WATER; XANTHAN GUM; DIETHYLHEXYL SYRINGYLIDENEMALONATE; EUCALYPTUS OIL; GLYCERYL STEARATE CITRATE; HELIANTHUS ANNUUS SEED WAX; CARBOMER COPOLYMER TYPE A (ALLYL PENTAERYTHRITOL CROSSLINKED); ARGAN OIL; MEDIUM-CHAIN TRIGLYCERIDES; CLOVE LEAF OIL; PLANTAGO LANCEOLATA LEAF; LAURYL LACTATE; ARGININE; POLYMETHYLSILSESQUIOXANE (4.5 MICRONS); CETOSTEARYL ALCOHOL; 1,2-HEXANEDIOL; CAPRYLYL GLYCOL; HYDROXYACETOPHENONE; PROPANEDIOL; CHINESE CINNAMON LEAF OIL; VANILLIN; COCO-GLYCERIDES; CETYL PHOSPHATE; DIISOPROPYL SEBACATE

Hand Screen Broad Spectrum Sunscreen SPF 40

Active Ingredients Purpose

Avobenzone 3% Sunscreen

Octisalate 5% Sunscreen

Octocrylene 10% Sunscreen

Uses

Helps Prevent Sunburn
If used as directed with other sun protection measures (see Directions), decreases the risk of skin cancer and early skin aging caused by the sun.

Keep out of reach of children

If swallowed, get medical help or contact a poison Control Center right away

Stop use and ask a doctor if rash occurs.

Warnings

For external use only.

Do not use on damaged or broken skin

When using this product keep out of eyes. Rinse with water to remove

Directions

- Apply generously and evenly 15 minutes before sun exposure
- Use a water-resistant sunscreen if swimming or sweating
- Reapply at least every 2 hours.
- Sun Protection Measures Spending time in the sun increases your risk of
- skin cancer and early skin aging. To decrease this risk, regularly use a
- sunscreen with a Broad-Spectrum SPF value of 15 or higher and other sun
- protection measures including: • limit your time in the sun, especially from 10
- a.m. – 2 p.m. • wear long-sleeved shirts, pants, hats, and sunglasses
- Children under 6 months of age: ask a doctor.

Inactive Ingredients

Water, Butyloctyl Salicylate, C12-15 Alkyl Benzoate, Cetearyl Alcohol, Propanediol, Glyceryl Stearate Citrate, Cocoglycerides, Isododecane, Cetyl Esters, Cetyl Phosphate, Diisopropyl Sebacate, Isodecyl Neopentanoate, Lauryl Lactate, Arginine, 1,2-Hexanediol, Caprylyl Glycol, Hydroxyacetophenone, Polymethylsilsequioxane, Raphanus Sativus (Radish) Seed Oil, Diethylhexyl syringylidenemalonate, Helianthuus Annuus (Sunflower) Seed Wax, Limnanthes Alba (Meadowfoam) Seed Oil, Acrylates/C10-30 Alkyl Acrylate Crosspolymer, Chlorphenesin, Xanthan Gum, Trisodium Ethylenediamine Disuccinate, Argania Spinosa Kernel Oil, Caprylic/Capric Triglyceride, Citrus Nobilis (Madarin Orange) Peel Oil, Plantago Lanceolata Leaf Extract, Glycine Soja (Soybean) Oil, Tocopherol, Cymbopogon Schoenanthus Oil, Hippophae Rhamnoides Fruit Oil, Elettaria Cardamomum Seed Oil, Eugenia Caryophyllus (Clove) Leaf Oil, Cinnamomum Cassia Leaf Oil, Vanillin, Eucalyptus Globulus Leaf Oil, Lavandula Hybrida Grosso Herb Oil

PACKAGE LABEL

Supergoop!

Handscreen SPF 40

Broad Spectrum Sunscreen SPF 40

1.0fl. oz./ 30 ml.